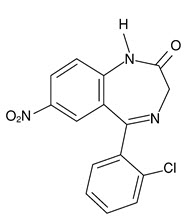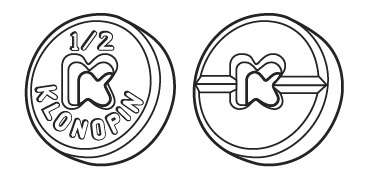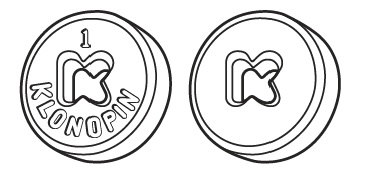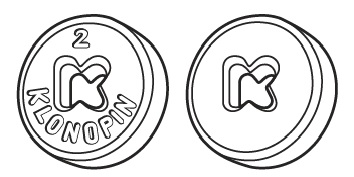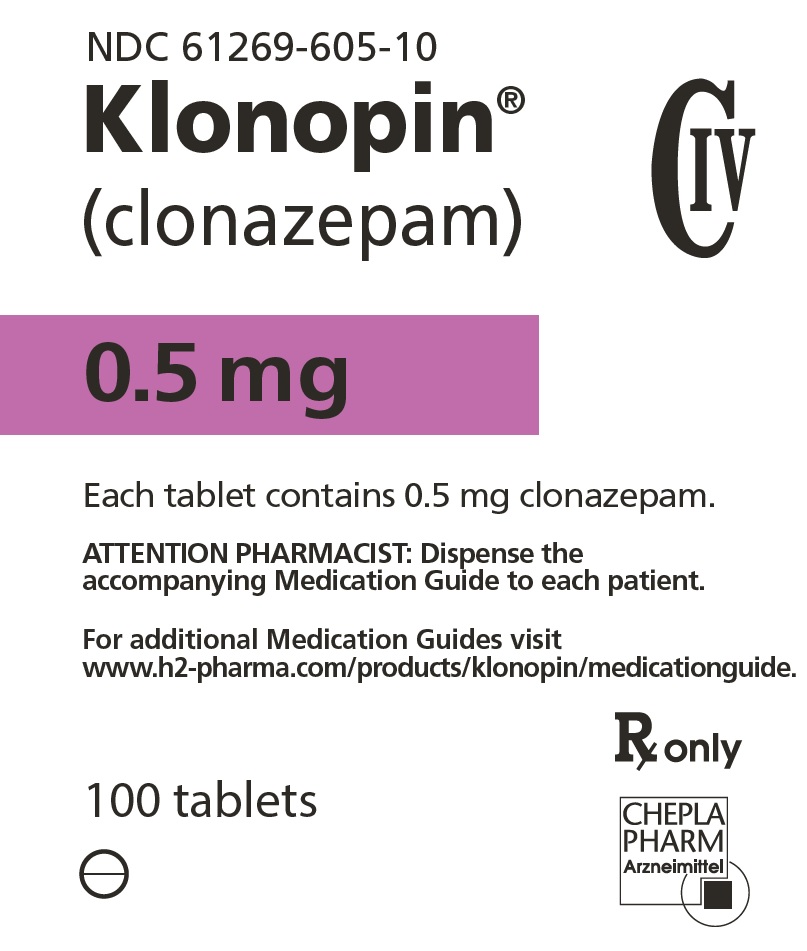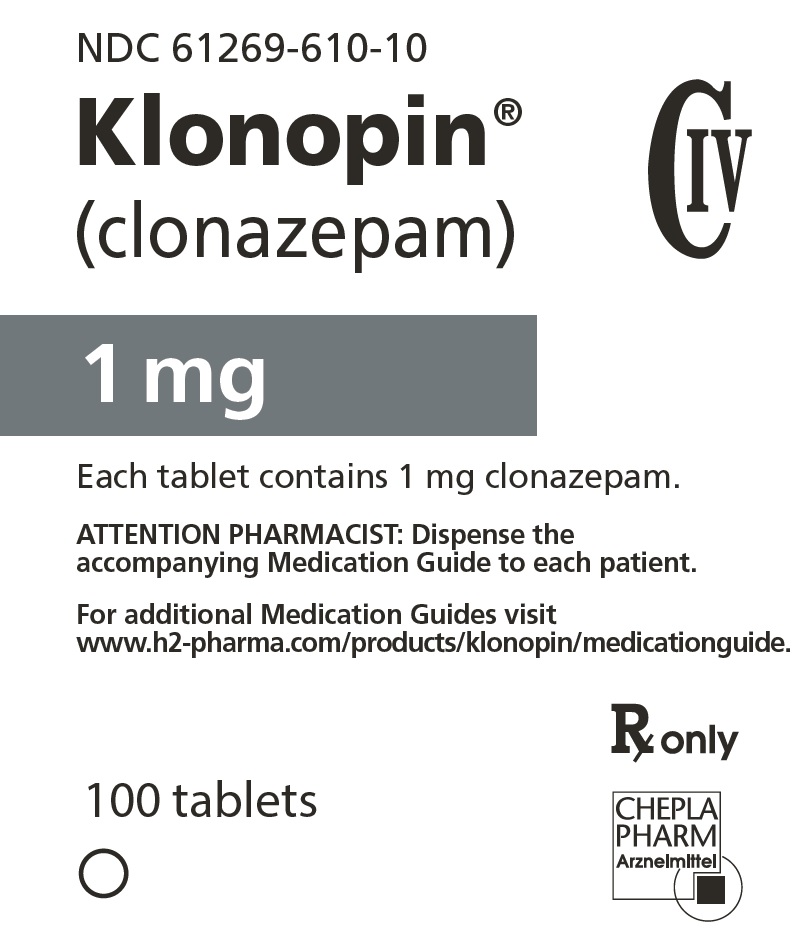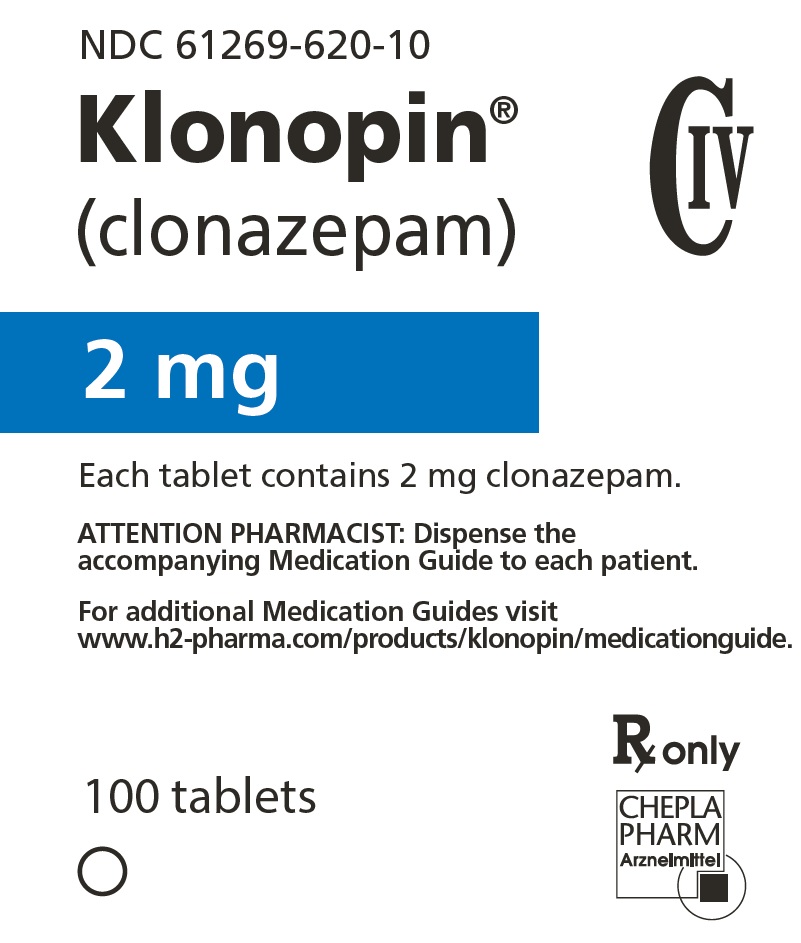 DRUG LABEL: Klonopin
NDC: 61269-605 | Form: TABLET
Manufacturer: H2-Pharma, LLC
Category: prescription | Type: HUMAN PRESCRIPTION DRUG LABEL
Date: 20251201
DEA Schedule: CIV

ACTIVE INGREDIENTS: CLONAZEPAM 0.5 mg/1 1
INACTIVE INGREDIENTS: LACTOSE, UNSPECIFIED FORM; MAGNESIUM STEARATE; MICROCRYSTALLINE CELLULOSE; STARCH, CORN; FD&C YELLOW NO. 6

KLONOPIN® TABLETS
(clonazepam)

CIV

Rx only

WARNING: RISKS FROM CONCOMITANT USE WITH OPIOIDS; ABUSE, MISUSE, AND ADDICTION; and DEPENDENCE AND WITHDRAWAL REACTIONS

- Concomitant use of benzodiazepines and opioids may result in profound sedation, respiratory depression, coma, and death. Reserve concomitant prescribing of these drugs for patients for whom alternative treatment options are inadequate. Limit dosages and durations to the minimum required. Follow patients for signs and symptoms of respiratory depression and sedation (see WARNINGS and PRECAUTIONS).
- The use of benzodiazepines, including Klonopin, exposes users to risks of abuse, misuse, and addiction, which can lead to overdose or death. Abuse and misuse of benzodiazepines commonly involve concomitant use of other medications, alcohol, and/or illicit substances, which is associated with an increased frequency of serious adverse outcomes. Before prescribing Klonopin and throughout treatment, assess each patient's risk for abuse, misuse, and addiction (see WARNINGS).
- The continued use of benzodiazepines, including Klonopin, may lead to clinically significant physical dependence. The risks of dependence and withdrawal increase with longer treatment duration and higher daily dose. Abrupt discontinuation or rapid dosage reduction of Klonopin after continued use may precipitate acute withdrawal reactions, which can be life-threatening. To reduce the risk of withdrawal reactions, use a gradual taper to discontinue Klonopin or reduce the dosage (see DOSAGE AND ADMINISTRATION and WARNINGS).

DESCRIPTION

Klonopin, a benzodiazepine, is available as scored tablets with a K-shaped perforation containing 0.5 mg of clonazepam and unscored tablets with a K-shaped perforation containing 1 mg or 2 mg of clonazepam. Each tablet also contains lactose, magnesium stearate, microcrystalline cellulose and corn starch, with the following colorants: 0.5 mg—FD&C Yellow No. 6 Lake; 1 mg—FD&C Blue No. 1 Lake and FD&C Blue No. 2 Lake.

Chemically, clonazepam is 5-(2-chlorophenyl)-1,3-dihydro-7-nitro-2H-1,4-benzodiazepin-2-one. It is a light yellow crystalline powder. It has a molecular weight of 315.72 and the following structural formula:

CLINICAL PHARMACOLOGY

Pharmacodynamics

The precise mechanism by which clonazepam exerts its antiseizure and antipanic effects is unknown, although it is believed to be related to its ability to enhance the activity of gamma aminobutyric acid (GABA), the major inhibitory neurotransmitter in the central nervous system.

Pharmacokinetics

Clonazepam is rapidly and completely absorbed after oral administration. The absolute bioavailability of clonazepam is about 90%. Maximum plasma concentrations of clonazepam are reached within 1 to 4 hours after oral administration. Clonazepam is approximately 85% bound to plasma proteins. Clonazepam is highly metabolized, with less than 2% unchanged clonazepam being excreted in the urine. Biotransformation occurs mainly by reduction of the 7-nitro group to the 4-amino derivative. This derivative can be acetylated, hydroxylated and glucuronidated. Cytochrome P-450 including CYP3A, may play an important role in clonazepam reduction and oxidation. The elimination half-life of clonazepam is typically 30 to 40 hours. Clonazepam pharmacokinetics are dose-independent throughout the dosing range. There is no evidence that clonazepam induces its own metabolism or that of other drugs in humans.

Pharmacokinetics in Demographic Subpopulations and in Disease States

Controlled studies examining the influence of gender and age on clonazepam pharmacokinetics have not been conducted, nor have the effects of renal or liver disease on clonazepam pharmacokinetics been studied. Because clonazepam undergoes hepatic metabolism, it is possible that liver disease will impair clonazepam elimination. Thus, caution should be exercised when administering clonazepam to these patients (see CONTRAINDICATIONS).

In children, clearance values of 0.42 ± 0.32 mL/min/kg (ages 2 – 18 years) and 0.88 ± 0.4 mL/min/kg (ages 7 – 12 years) were reported; these values decreased with increasing body weight. Ketogenic diet in children does not affect clonazepam concentrations.

Clinical Trials

Panic Disorder

The effectiveness of Klonopin in the treatment of panic disorder was demonstrated in two double-blind, placebo-controlled studies of adult outpatients who had a primary diagnosis of panic disorder (DSM-IIIR) with or without agoraphobia. In these studies, Klonopin was shown to be significantly more effective than placebo in treating panic disorder on change from baseline in panic attack frequency, the Clinician's Global Impression Severity of Illness Score and the Clinician's Global Impression Improvement Score.

Study 1 was a 9-week, fixed-dose study involving Klonopin doses of 0.5, 1, 2, 3 or 4 mg/day or placebo. This study was conducted in four phases: a 1-week placebo lead-in, a 3-week upward titration, a 6-week fixed dose, and a 7-week discontinuance phase. A significant difference from placebo was observed consistently only for the 1 mg/day group. The difference between the 1 mg dose group and placebo in reduction from baseline in the number of full panic attacks was approximately 1 panic attack per week. At endpoint, 74% of patients receiving clonazepam 1 mg/day were free of full panic attacks, compared to 56% of placebo-treated patients.

Study 2 was a 6-week, flexible-dose study involving Klonopin in a dose range of 0.5 to 4 mg/day or placebo. This study was conducted in three phases: a 1-week placebo lead-in, a 6-week optimal-dose, and a 6-week discontinuance phase. The mean clonazepam dose during the optimal dosing period was 2.3 mg/day. The difference between Klonopin and placebo in reduction from baseline in the number of full panic attacks was approximately 1 panic attack per week. At endpoint, 62% of patients receiving clonazepam were free of full panic attacks, compared to 37% of placebo-treated patients.

Subgroup analyses did not indicate that there were any differences in treatment outcomes as a function of race or gender.

INDICATIONS AND USAGE

Seizure Disorders

Klonopin is useful alone or as an adjunct in the treatment of the Lennox-Gastaut syndrome (petit mal variant), akinetic, and myoclonic seizures. In patients with absence seizures (petit mal) who have failed to respond to succinimides, Klonopin may be useful.

Some loss of effect may occur during the course of clonazepam treatment (see PRECAUTIONS: Loss of Effect).

Panic Disorder

Klonopin is indicated for the treatment of panic disorder, with or without agoraphobia, as defined in DSM-V. Panic disorder is characterized by the occurrence of unexpected panic attacks and associated concern about having additional attacks, worry about the implications or consequences of the attacks, and/or a significant change in behavior related to the attacks.

The efficacy of Klonopin was established in two 6- to 9-week trials in panic disorder patients whose diagnoses corresponded to the DSM-IIIR category of panic disorder (see CLINICAL PHARMACOLOGY: Clinical Trials).

Panic disorder (DSM-V) is characterized by recurrent unexpected panic attacks, i.e., a discrete period of intense fear or discomfort in which four (or more) of the following symptoms develop abruptly and reach a peak within 10 minutes: (1) palpitations, pounding heart or accelerated heart rate; (2) sweating; (3) trembling or shaking; (4) sensations of shortness of breath or smothering; (5) feeling of choking; (6) chest pain or discomfort; (7) nausea or abdominal distress; (8) feeling dizzy, unsteady, lightheaded or faint; (9) derealization (feelings of unreality) or depersonalization (being detached from oneself); (10) fear of losing control; (11) fear of dying; (12) paresthesias (numbness or tingling sensations); (13) chills or hot flushes.

The effectiveness of Klonopin in long-term use, that is, for more than 9 weeks, has not been systematically studied in controlled clinical trials. The physician who elects to use Klonopin for extended periods should periodically reevaluate the long-term usefulness of the drug for the individual patient (see DOSAGE AND ADMINISTRATION).

CONTRAINDICATIONS

Klonopin is contraindicated in patients with the following conditions:

- History of sensitivity to benzodiazepines
- Clinical or biochemical evidence of significant liver disease
- Acute narrow angle glaucoma (it may be used in patients with open angle glaucoma who are receiving appropriate therapy).

WARNINGS

Risks from Concomitant Use with Opioids

Concomitant use of benzodiazepines, including Klonopin, and opioids may result in profound sedation, respiratory depression, coma, and death. Because of these risks, reserve concomitant prescribing of benzodiazepines and opioids for patients for whom alternative treatment options are inadequate.

Observational studies have demonstrated that concomitant use of opioid analgesics and benzodiazepines increases the risk of drug-related mortality compared to use of opioids alone. If a decision is made to prescribe Klonopin concomitantly with opioids, prescribe the lowest effective dosages and minimum durations of concomitant use, and follow patients closely for signs and symptoms of respiratory depression and sedation. Advise both patients and caregivers about the risks of respiratory depression and sedation when Klonopin is used with opioids (see PRECAUTIONS: Information for Patients and PRECAUTIONS: Drug Interactions).

Abuse, Misuse, and Addiction

The use of benzodiazepines, including KLONOPIN, exposes users to the risks of abuse, misuse, and addiction, which can lead to overdose or death. Abuse and misuse of benzodiazepines often (but not always) involve the use of doses greater than the maximum recommended dosage and commonly involve concomitant use of other medications, alcohol, and/or illicit substances, which is associated with an increased frequency of serious adverse outcomes, including respiratory depression, overdose, or death (see DRUG ABUSE AND DEPENDENCE: Abuse).

Before prescribing KLONOPIN and throughout treatment, assess each patient's risk for abuse, misuse, and addiction (e.g., using a standardized screening tool). Use of KLONOPIN, particularly in patients at elevated risk, necessitates counseling about the risks and proper use of KLONOPIN along with monitoring for signs and symptoms of abuse, misuse, and addiction. Prescribe the lowest effective dosage; avoid or minimize concomitant use of CNS depressants and other substances associated with abuse, misuse, and addiction (e.g., opioid analgesics, stimulants); and advise patients on the proper disposal of unused drug. If a substance use disorder is suspected, evaluate the patient and institute (or refer them for) early treatment, as appropriate.

Dependence and Withdrawal Reactions

To reduce the risk of withdrawal reactions, use a gradual taper to discontinue KLONOPIN or reduce the dosage (a patient-specific plan should be used to taper the dose) (see DOSAGE AND ADMINISTRATION: Discontinuation or Dosage Reduction of KLONOPIN).

Patients at an increased risk of withdrawal adverse reactions after benzodiazepine discontinuation or rapid dosage reduction include those who take higher dosages, and those who have had longer durations of use.

Acute Withdrawal Reactions

The continued use of benzodiazepines, including KLONOPIN, may lead to clinically significant physical dependence. Abrupt discontinuation or rapid dosage reduction of KLONOPIN after continued use, or administration of flumazenil (a benzodiazepine antagonist) may precipitate acute withdrawal reactions, which can be life-threatening (e.g., seizures) (see DRUG ABUSE AND DEPENDENCE: Dependence).

Protracted Withdrawal Syndrome

In some cases, benzodiazepine users have developed a protracted withdrawal syndrome with withdrawal symptoms lasting weeks to more than 12 months (see DRUG ABUSE AND DEPENDENCE: Dependence).

Interference with Cognitive and Motor Performance

Since Klonopin produces CNS depression, patients receiving this drug should be cautioned against engaging in hazardous occupations requiring mental alertness, such as operating machinery or driving a motor vehicle. They should also be warned about the concomitant use of alcohol or other CNS-depressant drugs during Klonopin therapy (see PRECAUTIONS: Drug Interactions and PRECAUTIONS: Information for Patients).

Suicidal Behavior and Ideation

Antiepileptic drugs (AEDs), including Klonopin, increase the risk of suicidal thoughts or behavior in patients taking these drugs for any indication. Patients treated with any AED for any indication should be monitored for the emergence or worsening of depression, suicidal thoughts or behavior, and/or any unusual changes in mood or behavior.

Pooled analyses of 199 placebo-controlled clinical trials (mono- and adjunctive therapy) of 11 different AEDs showed that patients randomized to one of the AEDs had approximately twice the risk (adjusted Relative Risk 1.8, 95% CI:1.2, 2.7) of suicidal thinking or behavior compared to patients randomized to placebo. In these trials, which had a median treatment duration of 12 weeks, the estimated incidence rate of suicidal behavior or ideation among 27,863 AED-treated patients was 0.43% compared to 0.24% among 16,029 placebo-treated patients, representing an increase of approximately one case of suicidal thinking or behavior for every 530 patients treated. There were four suicides in drug-treated patients in the trials and none in placebo-treated patients, but the number is too small to allow any conclusion about drug effect on suicide.

The increased risk of suicidal thoughts or behavior with AEDs was observed as early as one week after starting drug treatment with AEDs and persisted for the duration of treatment assessed. Because most trials included in the analysis did not extend beyond 24 weeks, the risk of suicidal thoughts or behavior beyond 24 weeks could not be assessed.

The risk of suicidal thoughts or behavior was generally consistent among drugs in the data analyzed. The finding of increased risk with AEDs of varying mechanisms of action and across a range of indications suggests that the risk applies to all AEDs used for any indication. The risk did not vary substantially by age (5–100 years) in the clinical trials analyzed.

Table 1 shows absolute and relative risk by indication for all evaluated AEDs.

Table 1 Risk by Indication for Antiepileptic Drugs in the Pooled Analysis
Indication | Placebo Patients with Events Per 1000 Patients | Drug Patients with Events Per 1000 Patients | Relative Risk: Incidence of Events in Drug Patients/Incidence in Placebo Patients | Risk Difference: Additional Drug Patients with Events per 1000 Patients
Epilepsy | 1.0 | 3.4 | 3.5 | 2.4
Psychiatric | 5.7 | 8.5 | 1.5 | 2.9
Other | 1.0 | 1.8 | 1.9 | 0.9
Total | 2.4 | 4.3 | 1.8 | 1.9

The relative risk for suicidal thoughts or behavior was higher in clinical trials for epilepsy than in clinical trials for psychiatric or other conditions, but the absolute risk differences were similar for the epilepsy and psychiatric indications.

Anyone considering prescribing Klonopin or any other AED must balance the risk of suicidal thoughts or behavior with the risk of untreated illness. Epilepsy and many other illnesses for which AEDs are prescribed are themselves associated with morbidity and mortality and with an increased risk of suicidal thoughts and behavior. Should suicidal thoughts and behavior emerge during treatment, the prescriber needs to consider whether the emergence of these symptoms in any given patient may be related to the illness being treated.

Patients, their caregivers, and families should be informed that AEDs increase the risk of suicidal thoughts and behavior and should be advised of the need to be alert for the emergence or worsening of the signs and symptoms of depression, any unusual changes in mood or behavior, or the emergence of suicidal thoughts, behavior, or thoughts about self-harm. Behaviors of concern should be reported immediately to healthcare providers.

Neonatal Sedation and Withdrawal Syndrome

Use of Klonopin late in pregnancy can result in sedation (respiratory depression, lethargy, hypotonia) and/or withdrawal symptoms (hyperreflexia, irritability, restlessness, tremors, inconsolable crying, and feeding difficulties) in the neonate (see PRECAUTIONS: Pregnancy). Monitor neonates exposed to Klonopin during pregnancy or labor for signs of sedation and monitor neonates exposed to Klonopin during pregnancy for signs of withdrawal; manage these neonates accordingly.

PRECAUTIONS

General

Worsening of Seizures

When used in patients in whom several different types of seizure disorders coexist, Klonopin may increase the incidence or precipitate the onset of generalized tonic-clonic seizures (grand mal). This may require the addition of appropriate anticonvulsants or an increase in their dosages. The concomitant use of valproic acid and Klonopin may produce absence status.

Loss of Effect

In some studies, up to 30% of patients who initially responded have shown a loss of anticonvulsant activity, often within 3 months of administration. In some cases, dosage adjustment may reestablish efficacy.

Laboratory Testing During Long-Term Therapy

Periodic blood counts and liver function tests are advisable during long-term therapy with Klonopin.

Psychiatric and Paradoxical Reactions

Paradoxical reactions, such as agitation, irritability, aggression, anxiety, anger, nightmares, hallucinations, and psychoses are known to occur when using benzodiazepines (see ADVERSE REACTIONS: Psychiatric). Should this occur, the use of the drug should be discontinued gradually (see WARNINGS: Dependence and Withdrawal Reactions and DRUG ABUSE AND DEPENDENCE: Dependence). Paradoxical reactions are more likely to occur in children and in the elderly.

Caution in Renally Impaired Patients

Metabolites of Klonopin are excreted by the kidneys; to avoid their excess accumulation, caution should be exercised in the administration of the drug to patients with impaired renal function.

Hypersalivation

Klonopin may produce an increase in salivation. This should be considered before giving the drug to patients who have difficulty handling secretions.

Respiratory Depression

Klonopin may cause respiratory depression and should be used with caution in patients with compromised respiratory function (e.g., chronic obstructive pulmonary disease, sleep apnea).

Porphyria

Klonopin may have a porphyrogenic effect and should be used with care in patients with porphyria.

Information for Patients

A Klonopin Medication Guide must be given to the patient each time Klonopin is dispensed, as required by law. Patients should be instructed to take Klonopin only as prescribed. Physicians are advised to discuss the following issues with patients for whom they prescribe Klonopin:

Risks from Concomitant Use with Opioids

Inform patients and caregivers that potentially fatal additive effects may occur if Klonopin is used with opioids and not to use such drugs concomitantly unless supervised by a health care provider (see WARNINGS: Risks from Concomitant Use with Opioids and PRECAUTIONS: Drug Interactions).

Abuse, Misuse, and Addiction

Inform patients that the use of KLONOPIN, even at recommended dosages, exposes users to risks of abuse, misuse, and addiction, which can lead to overdose and death, especially when used in combination with other medications (e.g., opioid analgesics), alcohol, and/or illicit substances. Inform patients about the signs and symptoms of benzodiazepine abuse, misuse, and addiction; to seek medical help if they develop these signs and/or symptoms; and on the proper disposal of unused drug (see WARNINGS: Abuse, Misuse, and Addiction and DRUG ABUSE AND DEPENDENCE).

Withdrawal Reactions

Inform patients that the continued use of KLONOPIN may lead to clinically significant physical dependence and that abrupt discontinuation or rapid dosage reduction of KLONOPIN may precipitate acute withdrawal reactions, which can be life-threatening. Inform patients that in some cases, patients taking benzodiazepines have developed a protracted withdrawal syndrome with withdrawal symptoms lasting weeks to more than 12 months. Instruct patients that discontinuation or dosage reduction of KLONOPIN may require a slow taper (see WARNINGS: Dependence and Withdrawal Reactions and DRUG ABUSE AND DEPENDENCE).

Interference With Cognitive and Motor Performance

Because benzodiazepines have the potential to impair judgment, thinking or motor skills, patients should be cautioned about operating hazardous machinery, including automobiles, until they are reasonably certain that Klonopin therapy does not affect them adversely.

Suicidal Thinking and Behavior

Patients, their caregivers, and families should be counseled that AEDs, including Klonopin, may increase the risk of suicidal thoughts and behavior and should be advised of the need to be alert for the emergence or worsening of symptoms of depression, any unusual changes in mood or behavior, or the emergence of suicidal thoughts, behavior, or thoughts about self-harm. Behaviors of concern should be reported immediately to healthcare providers.

Pregnancy

Advise pregnant females that use of Klonopin late in pregnancy can result in sedation (respiratory depression, lethargy, hypotonia) and/or withdrawal symptoms (hyperreflexia, irritability, restlessness, tremors, inconsolable crying, and feeding difficulties) in newborns (see WARNINGS: Neonatal Sedation and Withdrawal Syndrome and PRECAUTIONS: Pregnancy). Instruct patients to inform their healthcare provider if they are pregnant. Encourage patients to enroll in the North American Antiepileptic Drug (NAAED) Pregnancy Registry if they become pregnant while taking Klonopin. This registry is collecting information about the safety of antiepileptic drugs during pregnancy (see PRECAUTIONS: Pregnancy).

Nursing

Instruct patients to inform their healthcare provider if they are breastfeeding or intend to breastfeed. Instruct breastfeeding patients who take Klonopin to monitor their infants for excessive sedation, poor feeding and poor weight gain, and to seek medical attention if they notice these signs (see PRECAUTIONS: Nursing Mothers).

Concomitant Medication

Patients should be advised to inform their physicians if they are taking, or plan to take, any prescription or over-the-counter drugs, since there is a potential for interactions.

Alcohol

Patients should be advised to avoid alcohol while taking Klonopin.

Drug Interactions

Effect of Concomitant Use of Benzodiazepines and Opioids

The concomitant use of benzodiazepines and opioids increases the risk of respiratory depression because of actions at different receptor sites in the CNS that control respiration. Benzodiazepines interact at GABAA sites, and opioids interact primarily at mu receptors. When benzodiazepines and opioids are combined, the potential for benzodiazepines to significantly worsen opioid-related respiratory depression exists. Limit dosage and duration of concomitant use of benzodiazepines and opioids, and follow patients closely for respiratory depression and sedation.

Effect of Clonazepam on the Pharmacokinetics of Other Drugs

Clonazepam does not appear to alter the pharmacokinetics of carbamazepine or phenobarbital. Clonazepam has the potential to influence concentrations of phenytoin. Monitoring of phenytoin concentration is recommended when clonazepam is co-administrated with phenytoin. The effect of clonazepam on the metabolism of other drugs has not been investigated.

Effect of Other Drugs on the Pharmacokinetics of Clonazepam

Literature reports suggest that ranitidine, an agent that decreases stomach acidity, does not greatly alter clonazepam pharmacokinetics.

In a study in which the 2 mg clonazepam orally disintegrating tablet was administered with and without propantheline (an anticholinergic agent with multiple effects on the GI tract) to healthy volunteers, the AUC of clonazepam was 10% lower and the Cmax of clonazepam was 20% lower when the orally disintegrating tablet was given with propantheline compared to when it was given alone.

The selective serotonin reuptake inhibitors sertraline (weak CYP3A4 inducer) and fluoxetine (CYP2D6 inhibitor), and the anti-epileptic drug felbamate (CYP2C19 inhibitor and CYP3A4 inducer) do not affect the pharmacokinetics of clonazepam. Cytochrome P-450 inducers, such as phenytoin, carbamazepine, lamotrigine, and phenobarbital induce clonazepam metabolism, causing an approximately 38% decrease in plasma clonazepam levels. Although clinical studies have not been performed, based on the involvement of the cytochrome P-450 3A family in clonazepam metabolism, inhibitors of this enzyme system, notably oral antifungal agents (e.g., fluconazole), should be used cautiously in patients receiving clonazepam because they may impair the metabolism of clonazepam leading to exaggerated concentrations and effects.

Pharmacodynamic Interactions

The CNS-depressant action of the benzodiazepine class of drugs may be potentiated by alcohol, narcotics, barbiturates, nonbarbiturate hypnotics, antianxiety agents, the phenothiazines, thioxanthene and butyrophenone classes of antipsychotic agents, monoamine oxidase inhibitors and the tricyclic antidepressants, and by other anticonvulsant drugs.

Carcinogenesis, Mutagenesis, Impairment of Fertility

Carcinogenesis

Carcinogenicity studies have not been conducted with clonazepam.

Mutagenesis

The data currently available are not sufficient to determine the genotoxic potential of clonazepam.

Impairment of Fertility

In a two-generation fertility study in which clonazepam was given orally to rats at 10 and 100 mg/kg/day, there was a decrease in the number of pregnancies and in the number of offspring surviving until weaning. The lowest dose tested is approximately 5 and 24 times the maximum recommended human dose (MRHD) of 20 mg/day for seizure disorders and 4 mg/day for panic disorder, respectively, on a body surface area (mg/m^2) basis.

Pregnancy

Pregnancy Exposure Registry

There is a pregnancy exposure registry that monitors pregnancy outcomes in women exposed to AEDs, such as Klonopin, during pregnancy. Healthcare providers are encouraged to recommend that pregnant women taking Klonopin enroll in the NAAED Pregnancy Registry by calling 1-888-233-2334 or online at http://www.aedpregnancyregistry.org/.

Risk Summary

Neonates born to mothers using benzodiazepines late in pregnancy have been reported to experience symptoms of sedation and/or neonatal withdrawal (see WARNINGS: Neonatal Sedation and Withdrawal Syndrome, and Clinical Considerations). Available data from published observational studies of pregnant women exposed to benzodiazepines do not report a clear association with benzodiazepines and major birth defects (see Data).

Administration of clonazepam to pregnant rabbits during the period of organogenesis resulted in developmental toxicity, including increased incidences of fetal malformations, at doses similar to or below therapeutic doses in patients (see Animal Data). Data for other benzodiazepines suggest the possibility of long-term effects on neurobehavioral and immunological function in animals following prenatal exposure to benzodiazepines at clinically relevant doses.

The background risk of major birth defects and miscarriage for the indicated population is unknown. All pregnancies have a background risk of birth defect, loss, or other adverse outcomes. In the U.S. general population, the estimated risk of major birth defects and of miscarriage in clinically recognized pregnancies is 2% to 4% and 15% to 20%, respectively.

Clinical Considerations

Fetal/Neonatal Adverse Reactions

Benzodiazepines cross the placenta and may produce respiratory depression, hypotonia and sedation in neonates. Monitor neonates exposed to Klonopin during pregnancy or labor for signs of sedation, respiratory depression, hypotonia, and feeding problems. Monitor neonates exposed to Klonopin during pregnancy for signs of withdrawal. Manage these neonates accordingly (see WARNINGS: Neonatal Sedation and Withdrawal Syndrome).

Data

Human Data

Published data from observational studies on the use of benzodiazepines during pregnancy do not report a clear association with benzodiazepines and major birth defects.

Although early studies reported an increased risk of congenital malformations with diazepam and chlordiazepoxide, there was no consistent pattern noted. In addition, the majority of more recent case-control and cohort studies of benzodiazepine use during pregnancy, which were adjusted for confounding exposures to alcohol, tobacco and other medications, have not confirmed these findings.

Animal Data

In three studies in which clonazepam was administered orally to pregnant rabbits at doses of 0.2, 1, 5, or 10 mg/kg/day during the period of organogenesis, a similar pattern of malformations (cleft palate, open eyelid, fused sternebrae and limb defects) was observed at all doses, in a low, non-dose-related incidence. The lowest dose tested is less than the maximum recommended human dose (MRHD) of 20 mg/day for seizure disorders and similar to the MRHD of 4 mg/day for panic disorder, on a mg/m^2 basis. Reductions in maternal weight gain occurred at doses of 5 mg/kg/day or greater and reduction in embryofetal growth occurred in one study at a dose of 10 mg/kg/day.
No adverse maternal or embryofetal effects were observed in mice or rats following oral administration of clonazepam during organogenesis of doses up to 15 or 40 mg/kg/day, respectively (4 and 20 times the MRHD of 20 mg/day for seizure disorders and 20 and 100 times the MRHD of 4 mg/day for panic disorder, respectively, on a mg/m^2 basis).
Data for other benzodiazepines suggest the possibility of adverse developmental effects (long-term effects on neurobehavioral and immunological function) in animals following prenatal exposure to benzodiazepines.

Nursing Mothers

Risk Summary

Clonazepam is excreted in human milk. There are reports of sedation, poor feeding and poor weight gain in infants exposed to benzodiazepines through breast milk. There are no data on the effects of clonazepam on milk production.
The developmental and health benefits of breastfeeding should be considered along with the mother's clinical need for Klonopin and any potential adverse effects on the breastfed infant from Klonopin or from the underlying maternal condition.

Clinical Considerations

Infants exposed to Klonopin through breast milk should be monitored for sedation, poor feeding and poor weight gain.

Pediatric Use

Because of the possibility that adverse effects on physical or mental development could become apparent only after many years, a benefit-risk consideration of the long-term use of Klonopin is important in pediatric patients being treated for seizure disorder (see INDICATIONS AND USAGE and DOSAGE AND ADMINISTRATION).

Safety and effectiveness in pediatric patients with panic disorder below the age of 18 have not been established.

Geriatric Use

Clinical studies of Klonopin did not include sufficient numbers of subjects aged 65 and over to determine whether they respond differently from younger subjects. Other reported clinical experience has not identified differences in responses between the elderly and younger patients. In general, dose selection for an elderly patient should be cautious, usually starting at the low end of the dosing range, reflecting the greater frequency of decreased hepatic, renal, or cardiac function, and of concomitant disease or other drug therapy.

Because clonazepam undergoes hepatic metabolism, it is possible that liver disease will impair clonazepam elimination. Metabolites of Klonopin are excreted by the kidneys; to avoid their excess accumulation, caution should be exercised in the administration of the drug to patients with impaired renal function. Because elderly patients are more likely to have decreased hepatic and/or renal function, care should be taken in dose selection, and it may be useful to assess hepatic and/or renal function at the time of dose selection.

Sedating drugs may cause confusion and over-sedation in the elderly; elderly patients generally should be started on low doses of Klonopin and observed closely.

ADVERSE REACTIONS

The adverse experiences for Klonopin are provided separately for patients with seizure disorders and with panic disorder.

Seizure Disorders

The most frequently occurring side effects of Klonopin are referable to CNS depression. Experience in treatment of seizures has shown that drowsiness has occurred in approximately 50% of patients and ataxia in approximately 30%. In some cases, these may diminish with time; behavior problems have been noted in approximately 25% of patients. Others, listed by system, including those identified during postapproval use of Klonopin are:

Cardiovascular: Palpitations

Dermatologic: Hair loss, hirsutism, skin rash, ankle and facial edema

Gastrointestinal: Anorexia, coated tongue, constipation, diarrhea, dry mouth, encopresis, gastritis, increased appetite, nausea, sore gums

Genitourinary: Dysuria, enuresis, nocturia, urinary retention

Hematopoietic: Anemia, leukopenia, thrombocytopenia, eosinophilia

Hepatic: Hepatomegaly, transient elevations of serum transaminases and alkaline phosphatase

Musculoskeletal: Muscle weakness, pains

Miscellaneous: Dehydration, general deterioration, fever, lymphadenopathy, weight loss or gain

Neurologic: Abnormal eye movements, aphonia, choreiform movements, coma, diplopia, dysarthria, dysdiadochokinesis, ''glassy-eyed'' appearance, headache, hemiparesis, hypotonia, nystagmus, respiratory depression, slurred speech, tremor, vertigo

Psychiatric: Confusion, depression, amnesia, hysteria, increased libido, insomnia, psychosis (the behavior effects are more likely to occur in patients with a history of psychiatric disturbances).

The following paradoxical reactions have been observed: irritability, aggression, agitation, nervousness, hostility, anxiety, sleep disturbances, nightmares, abnormal dreams, hallucinations.

Respiratory: Chest congestion, rhinorrhea, shortness of breath, hypersecretion in upper respiratory passages

Panic Disorder

Adverse events during exposure to Klonopin were obtained by spontaneous report and recorded by clinical investigators using terminology of their own choosing. Consequently, it is not possible to provide a meaningful estimate of the proportion of individuals experiencing adverse events without first grouping similar types of events into a smaller number of standardized event categories. In the tables and tabulations that follow, CIGY dictionary terminology has been used to classify reported adverse events, except in certain cases in which redundant terms were collapsed into more meaningful terms, as noted below.

The stated frequencies of adverse events represent the proportion of individuals who experienced, at least once, a treatment-emergent adverse event of the type listed. An event was considered treatment-emergent if it occurred for the first time or worsened while receiving therapy following baseline evaluation.

Adverse Findings Observed in Short-Term, Placebo-Controlled Trials

Adverse Events Associated with Discontinuation of Treatment

Overall, the incidence of discontinuation due to adverse events was 17% in Klonopin compared to 9% for placebo in the combined data of two 6- to 9-week trials. The most common events (≥1%) associated with discontinuation and a dropout rate twice or greater for Klonopin than that of placebo included the following:

Table 2 Most Common Adverse Events (≥1%) Associated with Discontinuation of Treatment
Adverse Event | Klonopin (N=574) | Placebo (N=294)
Somnolence | 7% | 1%
Depression | 4% | 1%
Dizziness | 1% | <1%
Nervousness | 1% | 0%
Ataxia | 1% | 0%
Intellectual Ability Reduced | 1% | 0%

Adverse Events Occurring at an Incidence of 1% or More among Klonopin-Treated Patients

Table 3 enumerates the incidence, rounded to the nearest percent, of treatment-emergent adverse events that occurred during acute therapy of panic disorder from a pool of two 6- to 9-week trials. Events reported in 1% or more of patients treated with Klonopin (doses ranging from 0.5 to 4 mg/day) and for which the incidence was greater than that in placebo-treated patients are included.

The prescriber should be aware that the figures in Table 3 cannot be used to predict the incidence of side effects in the course of usual medical practice where patient characteristics and other factors differ from those that prevailed in the clinical trials. Similarly, the cited frequencies cannot be compared with figures obtained from other clinical investigations involving different treatments, uses and investigators. The cited figures, however, do provide the prescribing physician with some basis for estimating the relative contribution of drug and nondrug factors to the side effect incidence in the population studied.

Table 3 Treatment-Emergent Adverse Event Incidence in 6- to 9-Week Placebo-Controlled Clinical Trials [Events reported by at least 1% of patients treated with Klonopin and for which the incidence was greater than that for placebo.]
Clonazepam Maximum Daily Dose
Adverse Event by Body System | <1mg n=96 % | 1-<2mg n=129 % | 2-<3mg n=113 % | ≥3mg n=235 % | All Klonopin Groups N=574 % | Placebo N=294 %
Central & Peripheral Nervous System
Somnolence [Indicates that the p-value for the dose-trend test (Cochran-Mantel-Haenszel) for adverse event incidence was ≤0.10.] | 26 | 35 | 50 | 36 | 37 | 10
Dizziness | 5 | 5 | 12 | 8 | 8 | 4
Coordination Abnormal | 1 | 2 | 7 | 9 | 6 | 0
Ataxia | 2 | 1 | 8 | 8 | 5 | 0
Dysarthria | 0 | 0 | 4 | 3 | 2 | 0
Psychiatric
Depression | 7 | 6 | 8 | 8 | 7 | 1
Memory Disturbance | 2 | 5 | 2 | 5 | 4 | 2
Nervousness | 1 | 4 | 3 | 4 | 3 | 2
Intellectual Ability Reduced | 0 | 2 | 4 | 3 | 2 | 0
Emotional Lability | 0 | 1 | 2 | 2 | 1 | 1
Libido Decreased | 0 | 1 | 3 | 1 | 1 | 0
Confusion | 0 | 2 | 2 | 1 | 1 | 0
Respiratory System
Upper Respiratory Tract Infection | 10 | 10 | 7 | 6 | 8 | 4
Sinusitis | 4 | 2 | 8 | 4 | 4 | 3
Rhinitis | 3 | 2 | 4 | 2 | 2 | 1
Coughing | 2 | 2 | 4 | 0 | 2 | 0
Pharyngitis | 1 | 1 | 3 | 2 | 2 | 1
Bronchitis | 1 | 0 | 2 | 2 | 1 | 1
Gastrointestinal System
Constipation | 0 | 1 | 5 | 3 | 2 | 2
Appetite Decreased | 1 | 1 | 0 | 3 | 1 | 1
Abdominal Pain | 2 | 2 | 2 | 0 | 1 | 1
Body as a Whole
Fatigue | 9 | 6 | 7 | 7 | 7 | 4
Allergic Reaction | 3 | 1 | 4 | 2 | 2 | 1
Musculoskeletal
Myalgia | 2 | 1 | 4 | 0 | 1 | 1
Resistance Mechanism Disorders
Influenza | 3 | 2 | 5 | 5 | 4 | 3
Urinary System
Micturition Frequency | 1 | 2 | 2 | 1 | 1 | 0
Urinary Tract Infection | 0 | 0 | 2 | 2 | 1 | 0
Vision Disorders
Blurred Vision | 1 | 2 | 3 | 0 | 1 | 1
Reproductive Disorders [Denominators for events in gender-specific systems are: n=240 (clonazepam), 102 (placebo) for male, and 334 (clonazepam), 192 (placebo) for female.]
Female Dysmenorrhea | 0 | 6 | 5 | 2 | 3 | 2
Colpitis | 4 | 0 | 2 | 1 | 1 | 1
Male Ejaculation Delayed | 0 | 0 | 2 | 2 | 1 | 0
Impotence | 3 | 0 | 2 | 1 | 1 | 0

Commonly Observed Adverse Events

Table 4 Incidence of Most Commonly Observed Adverse Events [Treatment-emergent events for which the incidence in the clonazepam patients was ≥5% and at least twice that in the placebo patients.] in Acute Therapy in Pool of 6- to 9-Week Trials
Adverse Event | Clonazepam (N=574) | Placebo (N=294)
Somnolence | 37% | 10%
Depression | 7% | 1%
Coordination Abnormal | 6% | 0%
Ataxia | 5% | 0%

Treatment-Emergent Depressive Symptoms

In the pool of two short-term placebo-controlled trials, adverse events classified under the preferred term "depression" were reported in 7% of Klonopin-treated patients compared to 1% of placebo-treated patients, without any clear pattern of dose relatedness. In these same trials, adverse events classified under the preferred term "depression" were reported as leading to discontinuation in 4% of Klonopin-treated patients compared to 1% of placebo-treated patients. While these findings are noteworthy, Hamilton Depression Rating Scale (HAM-D) data collected in these trials revealed a larger decline in HAM-D scores in the clonazepam group than the placebo group suggesting that clonazepam-treated patients were not experiencing a worsening or emergence of clinical depression.

Other Adverse Events Observed During the Premarketing Evaluation of Klonopin in Panic Disorder

Following is a list of modified CIGY terms that reflect treatment-emergent adverse events reported by patients treated with Klonopin at multiple doses during clinical trials. All reported events are included except those already listed in Table 3 or elsewhere in labeling, those events for which a drug cause was remote, those event terms which were so general as to be uninformative, and events reported only once and which did not have a substantial probability of being acutely life-threatening. It is important to emphasize that, although the events occurred during treatment with Klonopin, they were not necessarily caused by it.

Events are further categorized by body system and listed in order of decreasing frequency. These adverse events were reported infrequently, which is defined as occurring in 1/100 to 1/1000 patients.

Body as a Whole: weight increase, accident, weight decrease, wound, edema, fever, shivering, abrasions, ankle edema, edema foot, edema periorbital, injury, malaise, pain, cellulitis, inflammation localized

Cardiovascular Disorders: chest pain, hypotension postural

Central and Peripheral Nervous System Disorders: migraine, paresthesia, drunkenness, feeling of enuresis, paresis, tremor, burning skin, falling, head fullness, hoarseness, hyperactivity, hypoesthesia, tongue thick, twitching

Gastrointestinal System Disorders: abdominal discomfort, gastrointestinal inflammation, stomach upset, toothache, flatulence, pyrosis, saliva increased, tooth disorder, bowel movements frequent, pain pelvic, dyspepsia, hemorrhoids

Hearing and Vestibular Disorders: vertigo, otitis, earache, motion sickness

Heart Rate and Rhythm Disorders: palpitation

Metabolic and Nutritional Disorders: thirst, gout

Musculoskeletal System Disorders: back pain, fracture traumatic, sprains and strains, pain leg, pain nape, cramps muscle, cramps leg, pain ankle, pain shoulder, tendinitis, arthralgia, hypertonia, lumbago, pain feet, pain jaw, pain knee, swelling knee

Platelet, Bleeding and Clotting Disorders: bleeding dermal

Psychiatric Disorders: insomnia, organic disinhibition, anxiety, depersonalization, dreaming excessive, libido loss, appetite increased, libido increased, reactions decreased, aggression, apathy, disturbance in attention, excitement, anger, hunger abnormal, illusion, nightmares, sleep disorder, suicide ideation, yawning

Reproductive Disorders, Female: breast pain, menstrual irregularity

Reproductive Disorders, Male: ejaculation decreased

Resistance Mechanism Disorders: infection mycotic, infection viral, infection streptococcal, herpes simplex infection, infectious mononucleosis, moniliasis

Respiratory System Disorders: sneezing excessive, asthmatic attack, dyspnea, nosebleed, pneumonia, pleurisy

Skin and Appendages Disorders: acne flare, alopecia, xeroderma, dermatitis contact, flushing, pruritus, pustular reaction, skin burns, skin disorder

Special Senses Other, Disorders: taste loss

Urinary System Disorders: dysuria, cystitis, polyuria, urinary incontinence, bladder dysfunction, urinary retention, urinary tract bleeding, urine discoloration

Vascular (Extracardiac) Disorders: thrombophlebitis leg

Vision Disorders: eye irritation, visual disturbance, diplopia, eye twitching, styes, visual field defect, xerophthalmia

DRUG ABUSE AND DEPENDENCE

Controlled Substance

Klonopin contains clonazepam, a Schedule IV controlled substance.

Abuse

Klonopin is a benzodiazepine and a CNS depressant with a potential for abuse and addiction. Abuse is the intentional, non-therapeutic use of a drug, even once, for its desirable psychological or physiological effects. Misuse is the intentional use, for therapeutic purposes, of a drug by an individual in a way other than prescribed by a health care provider or for whom it was not prescribed. Drug addiction is a cluster of behavioral, cognitive, and physiological phenomena that may include a strong desire to take the drug, difficulties in controlling drug use (e.g., continuing drug use despite harmful consequences, giving a higher priority to drug use than other activities and obligations), and possible tolerance or physical dependence. Even taking benzodiazepines as prescribed may put patients at risk for abuse and misuse of their medication. Abuse and misuse of benzodiazepines may lead to addiction.

Abuse and misuse of benzodiazepines often (but not always) involve the use of doses greater than the maximum recommended dosage and commonly involve concomitant use of other medications, alcohol, and/or illicit substances, which is associated with an increased frequency of serious adverse outcomes, including respiratory depression, overdose, or death. Benzodiazepines are often sought by individuals who abuse drugs and other substances, and by individuals with addictive disorders (see WARNINGS: Abuse, Misuse, and Addiction).

The following adverse reactions have occurred with benzodiazepine abuse and/or misuse: abdominal pain, amnesia, anorexia, anxiety, aggression, ataxia, blurred vision, confusion, depression, disinhibition, disorientation, dizziness, euphoria, impaired concentration and memory, indigestion, irritability, muscle pain, slurred speech, tremors, and vertigo.

The following severe adverse reactions have occurred with benzodiazepine abuse and/or misuse: delirium, paranoia, suicidal ideation and behavior, seizures, coma, breathing difficulty, and death. Death is more often associated with polysubstance use (especially benzodiazepines with other CNS depressants such as opioids and alcohol).

Dependence

Physical Dependence

Klonopin may produce physical dependence from continued therapy. Physical dependence is a state that develops as a result of physiological adaptation in response to repeated drug use, manifested by withdrawal signs and symptoms after abrupt discontinuation or a significant dose reduction of a drug. Abrupt discontinuation or rapid dosage reduction of benzodiazepines or administration of flumazenil, a benzodiazepine antagonist, may precipitate acute withdrawal reactions, including seizures, which can be life-threatening. Patients at an increased risk of withdrawal adverse reactions after benzodiazepine discontinuation or rapid dosage reduction include those who take higher dosages (i.e., higher and/or more frequent doses) and those who have had longer durations of use (see WARNINGS: Dependence and Withdrawal Reactions).

To reduce the risk of withdrawal reactions, use a gradual taper to discontinue Klonopin or reduce the dosage (see DOSAGE AND ADMINISTRATION: Discontinuation or Dosage Reduction of Klonopin and WARNINGS: Dependence and Withdrawal Reactions).

Acute withdrawal signs and symptoms associated with benzodiazepines have included abnormal involuntary movements, anxiety, blurred vision, depersonalization, depression, derealization, dizziness, fatigue, gastrointestinal adverse reactions (e.g., nausea, vomiting, diarrhea, weight loss, decreased appetite), headache, hyperacusis, hypertension, irritability, insomnia, memory impairment, muscle pain and stiffness, panic attacks, photophobia, restlessness, tachycardia, and tremor. More severe acute withdrawal signs and symptoms, including life-threatening reactions, have included catatonia, convulsions, delirium tremens, depression, hallucinations, mania, psychosis, seizures, and suicidality.

Protracted withdrawal syndrome associated with benzodiazepines is characterized by anxiety, cognitive impairment, depression, insomnia, formication, motor symptoms (e.g., weakness, tremor, muscle twitches), paresthesia, and tinnitus that persists beyond 4 to 6 weeks after initial benzodiazepine withdrawal. Protracted withdrawal symptoms may last weeks to more than 12 months. As a result, there may be difficulty in differentiating withdrawal symptoms from potential re-emergence or continuation of symptoms for which the benzodiazepine was being used.

Tolerance

Tolerance to Klonopin may develop from continued therapy. Tolerance is a physiological state characterized by a reduced response to a drug after repeated administration (i.e., a higher dose of a drug is required to produce the same effect that was once obtained at a lower dose). Tolerance to the therapeutic effect of Klonopin may develop; however, little tolerance develops to the amnestic reactions and other cognitive impairments caused by benzodiazepines.

Following the short-term treatment of patients with panic disorder in Studies 1 and 2 (see CLINICAL PHARMACOLOGY: Clinical Trials), patients were gradually withdrawn during a 7-week downward-titration (discontinuance) period. Overall, the discontinuance period was associated with good tolerability and a very modest clinical deterioration, without evidence of a significant rebound phenomenon. However, there are not sufficient data from adequate and well-controlled long-term clonazepam studies in patients with panic disorder to accurately estimate the risks of withdrawal symptoms and dependence that may be associated with such use.

OVERDOSAGE

Overdosage of benzodiazepines is characterized by central nervous system depression ranging from drowsiness to coma. In mild to moderate cases, symptoms can include drowsiness, confusion, dysarthria, lethargy, hypnotic state, diminished reflexes, ataxia, and hypotonia. Rarely, paradoxical or disinhibitory reactions (including agitation, irritability, impulsivity, violent behavior, confusion, restlessness, excitement, and talkativeness) may occur. In severe overdosage cases, patients may develop respiratory depression and coma. Overdosage of benzodiazepines in combination with other CNS depressants (including alcohol and opioids) may be fatal (see WARNINGS: Abuse, Misuse, and Addiction). Markedly abnormal (lowered or elevated) blood pressure, heart rate, or respiratory rate raise the concern that additional drugs and/or alcohol are involved in the overdosage.

In managing benzodiazepine overdosage, employ general supportive measures, including intravenous fluids and airway maintenance. Flumazenil, a specific benzodiazepine receptor antagonist indicated for the complete or partial reversal of the sedative effects of benzodiazepines in the management of benzodiazepine overdosage, can lead to withdrawal and adverse reactions, including seizures, particularly in the context of mixed overdosage with drugs that increase seizure risk (e.g., tricyclic and tetracyclic antidepressants) and in patients with long-term benzodiazepine use and physical dependency. The risk of withdrawal seizures with flumazenil use may be increased in patients with epilepsy. Flumazenil is contraindicated in patients who have received a benzodiazepine for control of a potentially life-threatening condition (e.g., status epilepticus). If the decision is made to use flumazenil, it should be used as an adjunct to, not as a substitute for, supportive management of benzodiazepine overdosage. See the flumazenil injection Prescribing Information.

Consider contacting the Poison Help line (1-800-222-1222) or a medical toxicologist for additional overdosage management recommendations.

DOSAGE AND ADMINISTRATION

Clonazepam is available as a tablet. The tablets should be administered with water by swallowing the tablet whole.

Seizure Disorders

The use of multiple anticonvulsants may result in an increase of CNS depressant adverse effects. This should be considered before adding Klonopin to an existing anticonvulsant regimen.

Adults

The initial dose for adults with seizure disorders should not exceed 1.5 mg/day divided into three doses. Dosage may be increased in increments of 0.5 to 1 mg every 3 days until seizures are adequately controlled or until side effects preclude any further increase. Maintenance dosage must be individualized for each patient depending upon response. Maximum recommended daily dose is 20 mg.

Pediatric Patients

Klonopin is administered orally. In order to minimize drowsiness, the initial dose for infants and children (up to 10 years of age or 30 kg of body weight) should be between 0.01 and 0.03 mg/kg/day but not to exceed 0.05 mg/kg/day given in two or three divided doses. Dosage should be increased by no more than 0.25 to 0.5 mg every third day until a daily maintenance dose of 0.1 to 0.2 mg/kg of body weight has been reached, unless seizures are controlled or side effects preclude further increase. Whenever possible, the daily dose should be divided into three equal doses. If doses are not equally divided, the largest dose should be given before retiring.

Geriatric Patients

There is no clinical trial experience with Klonopin in seizure disorder patients 65 years of age and older. In general, elderly patients should be started on low doses of Klonopin and observed closely (see PRECAUTIONS: Geriatric Use).

Panic Disorder

Adults

The initial dose for adults with panic disorder is 0.25 mg twice daily. An increase to the target dose for most patients of 1 mg/day may be made after 3 days. The recommended dose of 1 mg/day is based on the results from a fixed dose study in which the optimal effect was seen at 1 mg/day. Higher doses of 2, 3 and 4 mg/day in that study were less effective than the 1 mg/day dose and were associated with more adverse effects. Nevertheless, it is possible that some individual patients may benefit from doses of up to a maximum dose of 4 mg/day, and in those instances, the dose may be increased in increments of 0.125 to 0.25 mg twice daily every 3 days until panic disorder is controlled or until side effects make further increases undesired. To reduce the inconvenience of somnolence, administration of one dose at bedtime may be desirable.

Treatment should be discontinued gradually, with a decrease of 0.125 mg twice daily every 3 days, until the drug is completely withdrawn.

There is no body of evidence available to answer the question of how long the patient treated with clonazepam should remain on it. Therefore, the physician who elects to use Klonopin for extended periods should periodically reevaluate the long-term usefulness of the drug for the individual patient.

Pediatric Patients

There is no clinical trial experience with Klonopin in panic disorder patients under 18 years of age.

Geriatric Patients

There is no clinical trial experience with Klonopin in panic disorder patients 65 years of age and older. In general, elderly patients should be started on low doses of Klonopin and observed closely (see PRECAUTIONS: Geriatric Use).

Discontinuation or Dosage Reduction of KLONOPIN

To reduce the risk of withdrawal reactions, increased seizure frequency, and status epilepticus, use a gradual taper to discontinue Klonopin or reduce the dosage. If a patient develops withdrawal reactions, consider pausing the taper or increasing the dosage to the previous tapered dosage level. Subsequently decrease the dosage more slowly (see WARNINGS: Dependence and Withdrawal Reactions and DRUG ABUSE AND DEPENDENCE: Dependence).

HOW SUPPLIED

Klonopin tablets are available as scored tablets with a K-shaped perforation—0.5 mg, orange (NDC 61269-605-10); and unscored tablets with a K-shaped perforation—1 mg, blue (NDC 61269-610-10); 2 mg, white (NDC 61269-620-10)—bottles of 100.

Imprint on tablets:

0.5 mg | — | 1/2 KLONOPIN (front) No imprint (scored side)
1 mg | — | 1 KLONOPIN (front) No imprint (reverse side)
2 mg | — | 2 KLONOPIN (front) No imprint (reverse side)

STORAGE AND HANDLING

Store at 25°C (77°F); excursions permitted to 15° to 30°C (59° to 86°F).

Distributed by:

H2-Pharma, LLC
Montgomery, AL
36117, USA

Licensed by:

CHEPLAPHARM Arzneimittel GmbH
Ziegelhof 24, 17489 Greifswald
Germany

Revised: 1/2023

© 2021 CHEPLAPHARM Arzneimittel GmbH

All rights reserved.

MEDICATION GUIDE
KLONOPIN (KLON-oh-pin) (clonazepam)
tablets, for oral use, CIV

What is the most important information I should know about KLONOPIN?

- KLONOPIN is a benzodiazepine medicine. Taking benzodiazepines with opioid medicines, alcohol, or other central nervous system (CNS) depressants (including street drugs) can cause severe drowsiness, breathing problems (respiratory depression), coma, and death.Get emergency help right away if any of the following happens:
  - shallow or slowed breathing
  - breathing stops (which may lead to the heart stopping)
  - excessive sleepiness (sedation)
  Do not drive or operate heavy machinery until you know how taking KLONOPIN and opioids affects you.

- Risk of abuse, misuse, and addiction.There is a risk of abuse, misuse, and addiction with benzodiazepines, including KLONOPIN, which can lead to overdose and serious side effects including coma and death.
  - Serious side effects including coma and death have happened in people who have abused or misused benzodiazepines, including KLONOPIN. These serious side effects may also include delirium, paranoia, suicidal thoughts or actions, seizures, and difficulty breathing. Call your healthcare provider or go to the nearest hospital emergency room right away if you get any of these serious side effects.
  - You can develop an addiction even if you take KLONOPIN as prescribed by your healthcare provider.
  - Take KLONOPIN exactly as your healthcare provider prescribed.
  - Do not share your KLONOPIN with other people.
  - Keep KLONOPIN in a safe place and away from children.
- Physical dependence and withdrawal reactions.KLONOPIN can cause physical dependence and withdrawal reactions.
  - Do not suddenly stop taking KLONOPIN. Stopping KLONOPIN suddenly can cause serious and life-threatening side effects, including, unusual movements, responses, or expressions, seizures, sudden and severe mental or nervous system changes, depression, seeing or hearing things that others do not see or hear, an extreme increase in activity or talking, losing touch with reality, and suicidal thoughts or actions. Call your healthcare provider or go to the nearest hospital emergency room right away if you get any of these symptoms.
  - Some people who suddenly stop benzodiazepines have symptoms that can last for several weeks to more than 12 months, including, anxiety, trouble remembering, learning, or concentrating, depression, problems sleeping, feeling like insects are crawling under your skin, weakness, shaking, muscle twitching, burning or prickling feeling in your hands, arms, legs or feet, and ringing in your ears.
  - Physical dependence is not the same as drug addiction. Your healthcare provider can tell you more about the differences between physical dependence and drug addiction.
  - Do not take more KLONOPIN than prescribed or take KLONOPIN for longer than prescribed.
- KLONOPIN can make you sleepy or dizzy and can slow your thinking and motor skills. This may get better over time.
  - Do not drive, operate heavy machinery, or do other dangerous activities until you know how KLONOPIN affects you.
  - KLONOPIN may cause problems with your coordination, especially when you are walking or picking things up.
- Do not drink alcohol or take other drugs that may make you sleepy or dizzy while taking KLONOPIN until you talk to your healthcare provider. When taken with alcohol or drugs that cause sleepiness or dizziness, KLONOPIN may make your sleepiness or dizziness worse.
- Like other antiepileptic medicines, KLONOPIN may cause suicidal thoughts or actions in a very small number of people, about 1 in 500.
  Call your healthcare provider right away if you have any of these symptoms, especially if they are new, worse, or worry you:

- thoughts about suicide or dying
- new or worse anxiety
- trouble sleeping (insomnia)
- acting on dangerous impulses

- attempts to commit suicide
- feeling agitated or restless
- new or worse irritability
- an extreme increase in activity and talking (mania)

- new or worse depression
- panic attacks
- acting aggressive, being angry, or violent
- other unusual changes in behavior or mood

How can I watch for early symptoms of suicidal thoughts and actions?

- Pay attention to any changes, especially sudden changes, in mood, behaviors, thoughts, or feelings.
- Keep all follow-up visits with your healthcare provider as scheduled.

Call your healthcare provider between visits as needed, especially if you are worried about symptoms.
Suicidal thoughts or actions can be caused by things other than medicines. If you have suicidal thoughts or actions, your healthcare provider may check for other causes.

- Do not stop KLONOPIN without first talking to a healthcare provider.
  - Stopping KLONOPIN suddenly can cause serious problems. Stopping KLONOPIN suddenly can cause seizures that will not stop (status epilepticus).

What is KLONOPIN?

- KLONOPIN is a prescription medicine used alone or with other medicines to treat:
  - certain types of seizure disorders (epilepsy) in adults and children
  - panic disorder with or without fear of open spaces (agoraphobia) in adults
- KLONOPIN is a federally controlled substance (C-IV) because it contains clonazepam that can be abused or lead to dependence. Keep KLONOPIN in a safe place to prevent misuse and abuse. Selling or giving away KLONOPIN may harm others, and is against the law. Tell your healthcare provider if you have ever abused or been dependent on alcohol, prescription medicines, or street drugs.

It is not known if KLONOPIN is safe or effective in treating panic disorder in children younger than 18 years old.

Who should not take KLONOPIN?
Do not take KLONOPIN if you:

- are allergic to benzodiazepines
- have significant liver disease
- have an eye disease called acute narrow angle glaucoma

Ask your healthcare provider if you are not sure if you have any of the problems listed above.

Before you take KLONOPIN, tell your healthcare provider if you:

- have liver or kidney problems
- have lung problems (respiratory disease)
- have or have had depression, mood problems, or suicidal thoughts or behavior
- have any other medical problems
- are pregnant or plan to become pregnant.
  o Taking KLONOPIN late in pregnancy may cause your baby to have symptoms of sedation (breathing problems, sluggishness, low muscle tone), and/or withdrawal symptoms (jitteriness, irritability, restlessness, shaking, excessive crying, feeding problems).
  o Tell your healthcare provider right away if you become pregnant or think you are pregnant during treatment with KLONOPIN.
  o If you become pregnant while taking KLONOPIN, talk to your healthcare provider about registering with the North American Antiepileptic Drug Pregnancy Registry. You can register by calling 1-888-233-2334. The purpose of this registry is to collect information about the safety of antiepileptic drugs during pregnancy.
- are breastfeeding or plan to breastfeed. KLONOPIN can pass into breast milk.
  o Breastfeeding during treatment with KLONOPIN may cause your baby to have sleepiness, feeding problems, and decreased weight gain.
  o Talk to your healthcare provider about the best way to feed your baby while you take KLONOPIN.

Tell your healthcare provider about all the medicines you take, including prescription and over-the-counter medicines, vitamins, and herbal supplements.
Taking KLONOPIN with certain other medicines can cause side effects or affect how well KLONOPIN or the other medicines work. Do not start or stop other medicines without talking to your healthcare provider.

How should I take KLONOPIN?

- Take KLONOPIN exactly as your healthcare provider tells you. If you take KLONOPIN for seizures, your healthcare provider may change the dose until you are taking the right amount of medicine to control your symptoms.
- KLONOPIN is available as a tablet.
- Do not stop taking KLONOPIN without first talking to your healthcare provider. Stopping KLONOPIN suddenly can cause serious problems.
- KLONOPIN tablets should be taken with water and swallowed whole.
- If you take too much KLONOPIN, call your healthcare provider or local Poison Control Center right away.

What should I avoid while taking KLONOPIN?

- KLONOPIN can slow your thinking and motor skills. Do not drive, operate heavy machinery, or do other dangerous activities until you know how KLONOPIN affects you.
- Do not drink alcohol or take other medicines that may make you sleepy or dizzy while taking KLONOPIN until you talk to your healthcare provider. When taken with alcohol or medicines that cause sleepiness or dizziness, KLONOPIN may make your sleepiness or dizziness much worse.

What are the possible side effects of KLONOPIN?
See "What is the most important information I should know about KLONOPIN?"
KLONOPIN can also make your seizures happen more often or make them worse. Call your healthcare provider right away if your seizures get worse while taking KLONOPIN.
The most common side effects of KLONOPIN include:

- drowsiness
- problems with walking and coordination

- dizziness
- depression

- fatigue
- problems with memory

These are not all the possible side effects of KLONOPIN. Call your doctor for medical advice about side effects. You may report side effects to FDA at 1-800-FDA-1088. You may also report side effects to the Safety Call Center at 1-866-788-3904.

How should I store KLONOPIN?

- Store KLONOPIN between 59°F to 86°F (15°C to 30°C)
- Keep KLONOPIN and all medicines out of the reach of children

General Information about the safe and effective use of KLONOPIN
Medicines are sometimes prescribed for purposes other than those listed in a Medication Guide. Do not use KLONOPIN for a condition for which it was not prescribed. Do not give KLONOPIN to other people, even if they have the same symptoms that you have. It may harm them.
You can ask your pharmacist or healthcare provider for information about KLONOPIN that is written for health professionals.

What are the ingredients in KLONOPIN?
Active ingredient: clonazepam
Inactive ingredients:
Tablets:

- 0.5 mg tablets contain lactose, magnesium stearate, microcrystalline cellulose, corn starch, FD&C Yellow No. 6 Lake
- 1 mg tablets contain lactose, magnesium stearate, microcrystalline cellulose, corn starch, FD&C Blue No. 1 Lake and FD&C Blue No. 2 Lake
- 2 mg tablets contain lactose, magnesium stearate, microcrystalline cellulose, corn starch

Distributed by:
H2-Pharma, LLC
Montgomery, AL
36117, USA

Licensed by:
CHEPLAPHARM Arzneimittel GmbH
Ziegelhof 24, 17489 Greifswald
Germany

© 2021 CHEPLAPHARM Arzneimittel GmbH All rights reserved.

For additional Medication Guides, go to www.h2-pharma.com/products/klonopin/medicationguide.

This Medication Guide has been approved by the U.S. Food and Drug Administration.

Revised: 1/2023

Representative sample of labeling (see the HOW SUPPLIED section for complete listing):

PRINCIPAL DISPLAY PANEL - 0.5 mg Tablet Bottle Label

NDC 61269-605-10

Klonopin®
(clonazepam)
CIV

0.5 mg

Each tablet contains 0.5 mg clonazepam.

ATTENTION PHARMACIST: Dispense the
accompanying Medication Guide to each patient.

For additional Medication Guides visit
www.h2-pharma.com/products/klonopin/medicationguide.

100 tablets

Rx only

CHEPLAPHARM Arzneimittel

PRINCIPAL DISPLAY PANEL - 1 mg Tablet Bottle Label

NDC 61269-610-10

Klonopin®
(clonazepam)
CIV

1 mg

Each tablet contains 1 mg clonazepam.

ATTENTION PHARMACIST: Dispense the
accompanying Medication Guide to each patient.

For additional Medication Guides visit
www.h2-pharma.com/products/klonopin/medicationguide.

100 tablets

Rx only

CHEPLAPHARM Arzneimittel

PRINCIPAL DISPLAY PANEL - 2 mg Tablet Bottle Label

NDC 61269-620-10

Klonopin®
(clonazepam)
CIV

2 mg

Each tablet contains 2 mg clonazepam.

ATTENTION PHARMACIST: Dispense the
accompanying Medication Guide to each patient.

For additional Medication Guides visit
www.h2-pharma.com/products/klonopin/medicationguide.

100 tablets

Rx only

CHEPLAPHARM Arzneimittel